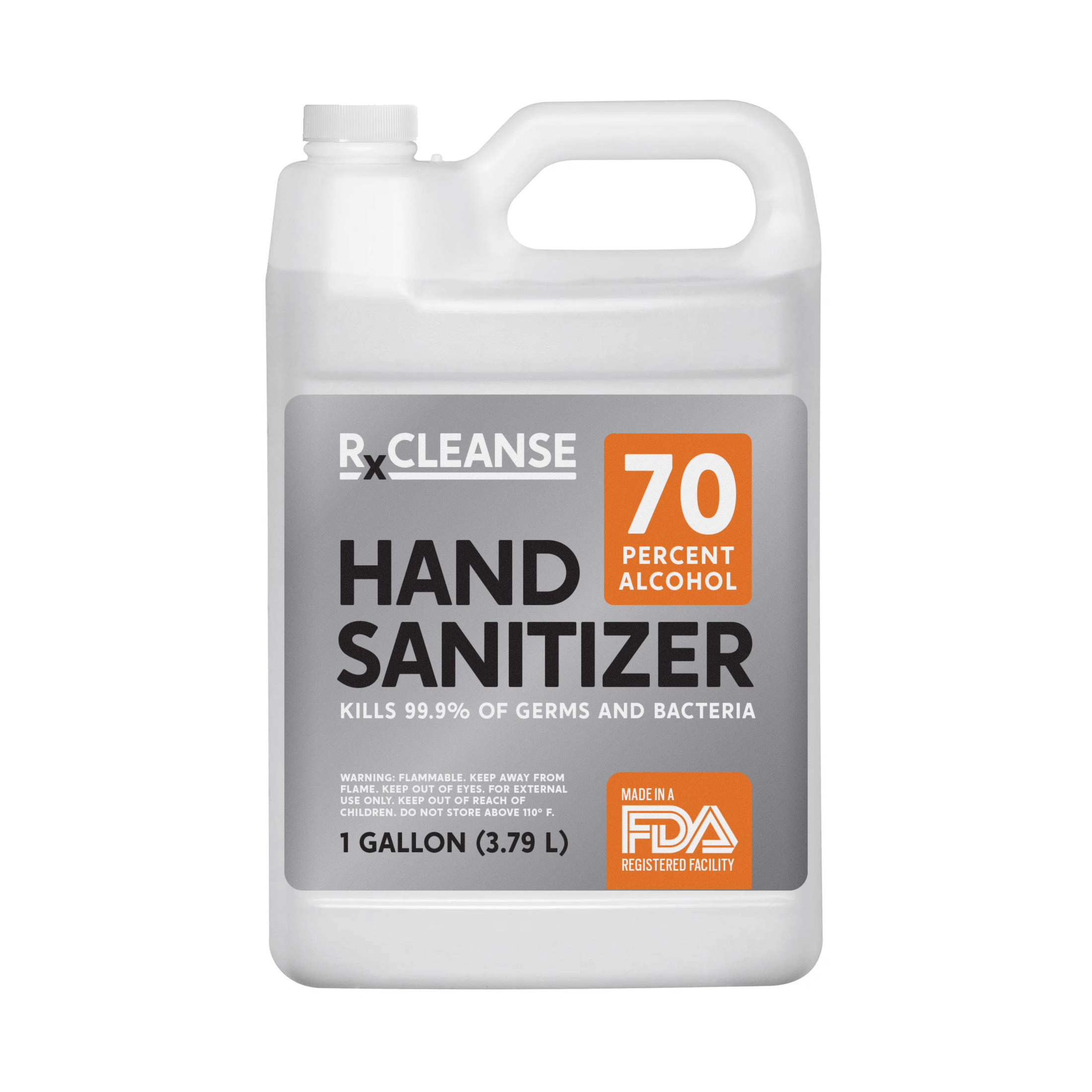 DRUG LABEL: RX Cleanse Hand Sanitizer
NDC: 74321-100 | Form: GEL
Manufacturer: 360 Labs, Inc.
Category: otc | Type: HUMAN OTC DRUG LABEL
Date: 20200513

ACTIVE INGREDIENTS: ALCOHOL 70 mL/100 mL
INACTIVE INGREDIENTS: CARBOMER HOMOPOLYMER, UNSPECIFIED TYPE 0.002 mL/100 mL; TROLAMINE 0.004 mL/100 mL; PEPPERMINT OIL 0.994 mL/100 mL; ALOE VERA LEAF 0.001 mL/100 mL; TEA TREE OIL 0.0004 mL/100 mL; GLYCERIN 0.04 mL/100 mL; WATER 21 mL/100 mL

Rx Cleanse Hand Sanitizer - Sample Not for Resale

Active Ingredient(s)

Alcohol 70% v/v. Purpose: Antiseptic

Purpose

Antiseptic, Hand Sanitizer

Use

Hand Sanitizer to help reduce bacteria that potentially can cause disease. For use when soap and water are not available.

Warnings

For external use only. Flammable. Keep away from heat or flame

Do not use

- in children less than 2 months of age
- on open skin wounds

When using this product keep out of eyes, ears, and mouth. In case of contact with eyes, rinse eyes thoroughly with water.
Stop use and ask a doctor if irritation or rash occurs. These may be signs of a serious condition.
Keep out of reach of children. If swallowed, get medical help or contact a Poison Control Center right away.

Stop use and ask a doctor if irritation or rash occurs. These may be signs of a serious condition.

Keep out of reach of children. If swallowed, get medical help or contact a Poison Control Center right away.

Directions

- Place enough product on hands to cover all surfaces. Rub hands together until dry.
- Supervise children under 6 years of age when using this product to avoid swallowing.

Other information

- Store between 15-30C (59-86F)
- Avoid freezing and excessive heat above 40C (104F)

Inactive ingredients

Water (aqua), Glycerin, Carbomer, Triethanolamine, Aloe Barbadensis Leaf Juice, Peppermint Oil, Tea Tree Oil.

Package Label - Principal Display Panel

3.79L NDC: 74321-100-01

RX Cleanse Hand Sanitizer 70% Alcohol

Kills 99% of Germs and Bacteria

Made in a FDA Registered Facility

Warning: Flammable. Keep away from flame, keep out of eyes, for external use only. Keep out of reach from children. Do not store above 110 F